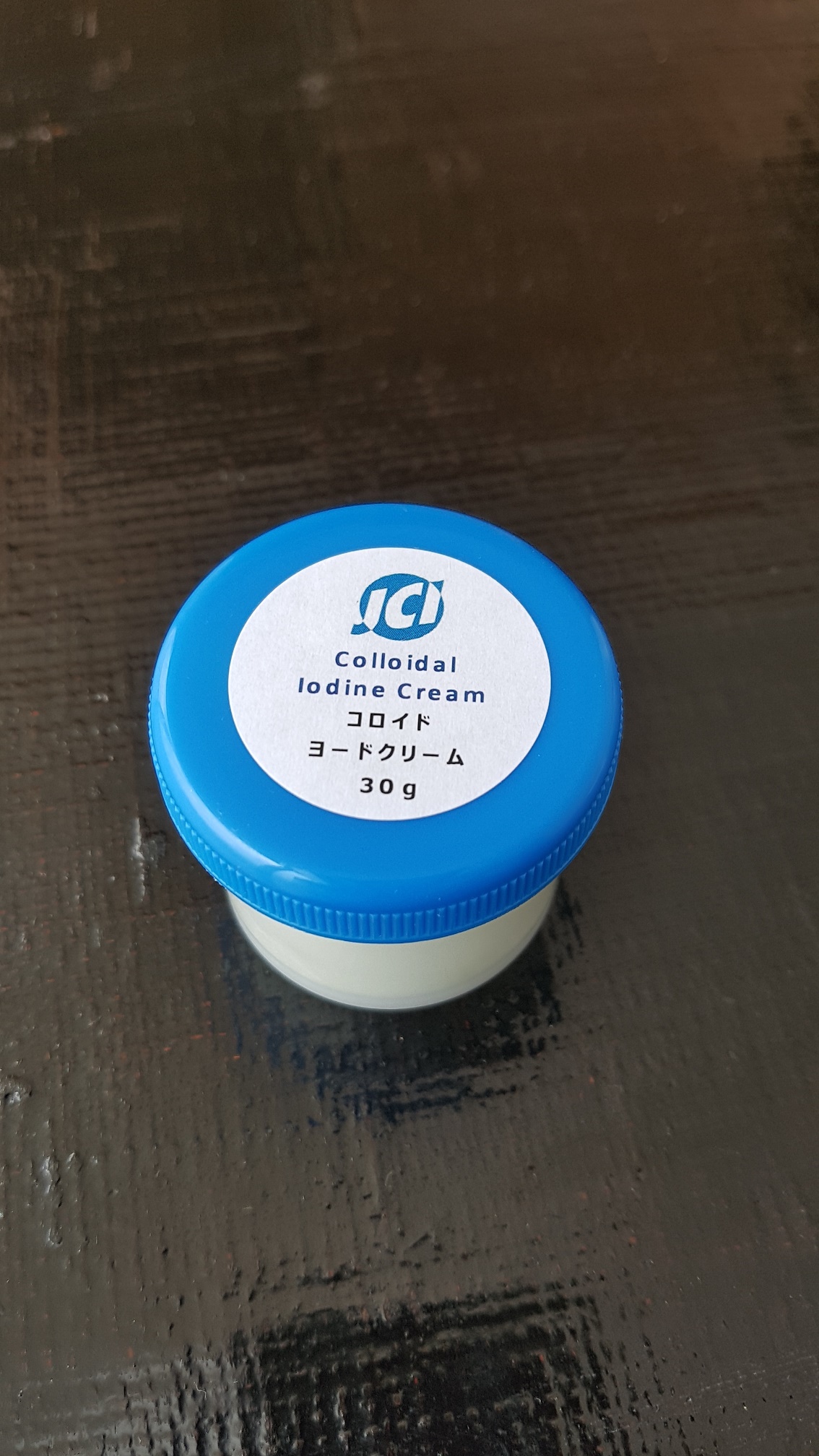 DRUG LABEL: Colloidal Iodine
NDC: 69164-1001 | Form: CREAM
Manufacturer: JCI INSTITUTE OF MEDICAL SCIENCE
Category: otc | Type: HUMAN OTC DRUG LABEL
Date: 20180521

ACTIVE INGREDIENTS: GLYCERIN 1 g/100 mL
INACTIVE INGREDIENTS: SORBITOL; DIMETHICONE; JOJOBA OIL; THREONINE

Drug Facts

ACTIVE INGREDIENT

glycerin

INACTIVE INGREDIENT

water, sorbitol, glyceryl stearate, isopropyl palmitate, stearic acid, dimethicone, mineral oil, malmiticacid, aloe barbadensis leaf ext, squalane oil, jojoba oil, rosemary oil, pca-na, betaine, serine, glutamic acid, alanine, lycine, arginine, threonine, proline, aminocaproic acid, methylparaben, propylparaben, phenoxyethanol, sodiumhydrogen-n(-1-oxooctadecyl)-L glutamate, sodium copper-chlorophyllin, sodium iodide

PURPOSE

skin ailments
external lesion on the skin
lesion on the scalp
secondary infectin of the lesions described on the above
female external genitals
functionality change on the skin
cosmetic use as basic lotion
diseases of oral cavity

keep out of reach of the children

INDICATIONS AND USAGE

apply the cream to the diseased part
adjust the number of times being applying the cream, depending on symptom
it is better to increase the number of times for the quick recovery
for the oral disease, it is recommended to mop the cream after applying the medium dose several times a day

do not use for ophthalmology because the safety for such use is not yet examined
keep in a room temperature
keep out of the direct sunlight

DOSAGE AND ADMINISTRATION

topical use only